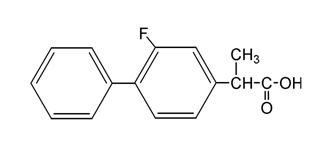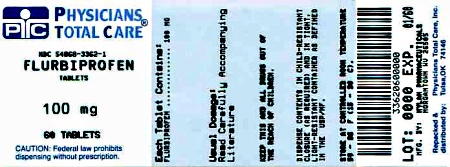 DRUG LABEL: Flurbiprofen
NDC: 54868-3362 | Form: TABLET, FILM COATED
Manufacturer: Physicians Total Care, Inc.
Category: prescription | Type: HUMAN PRESCRIPTION DRUG LABEL
Date: 20120612

ACTIVE INGREDIENTS: FLURBIPROFEN 100 mg/1 1
INACTIVE INGREDIENTS: SILICON DIOXIDE; CROSCARMELLOSE SODIUM; HYPROMELLOSES; ANHYDROUS LACTOSE; MAGNESIUM STEARATE; CELLULOSE, MICROCRYSTALLINE; POLYDEXTROSE; POLYETHYLENE GLYCOLS; SODIUM LAURYL SULFATE; TITANIUM DIOXIDE; TRIACETIN; FERRIC OXIDE YELLOW; FERROSOFERRIC OXIDE

BOXED WARNING

Cardiovascular Risk

- NSAIDs may cause an increased risk of serious cardiovascular thrombotic events, myocardial infarction, and stroke, which can be fatal. This risk may increase with duration of use. Patients with cardiovascular disease or risk factors for cardiovascular disease may be at greater risk (see WARNINGS).
- Flurbiprofen is contraindicated for the treatment of perioperative pain in the setting of coronary artery bypass graft (CABG) surgery (see WARNINGS).

Gastrointestinal Risk

- NSAIDs cause an increased risk of serious gastrointestinal adverse events including bleeding, ulceration, and perforation of the stomach or intestines, which can be fatal. These events can occur at any time during use and without warning symptoms. Elderly patients are at greater risk for serious gastrointestinal events (see WARNINGS).

DESCRIPTION

Flurbiprofen is a member of the phenylalkanoic acid derivative group of non-steroidal anti-inflammatory drugs. Flurbiprofen tablets are beige, round, film-coated tablets for oral administration. Flurbiprofen is a racemic mixture of (+)S- and (-)R-enantiomers. Flurbiprofen, USP is a white or slightly yellow crystalline powder. It is slightly soluble in water at pH 7.0 and readily soluble in most polar solvents. The chemical name is [1,1’-biphenyl]-4-acetic acid, 2-fluoro-alpha-methyl-, (±)-. The molecular weight is 244.26. Its molecular formula is C15H13FO2 and it has the following structural formula:

Each tablet, for oral administration, contains 50 mg or 100 mg flurbiprofen, USP. Inactive ingredients are colloidal silicon dioxide, croscarmellose sodium, hypromellose, lactose (anhydrous), magnesium stearate, microcrystalline cellulose, polydextrose, polyethylene glycol, sodium lauryl sulfate, titanium dioxide, triacetin, yellow iron oxide and black iron oxide.

CLINICAL PHARMACOLOGY

Pharmacodynamics

Flurbiprofen is a non-steroidal anti-inflammatory drug that exhibits anti-inflammatory, analgesic, and antipyretic activities in animal models. The mechanism of action of flurbiprofen, like that of other non-steroidal anti-inflammatory drugs, is not completely understood but may be related to prostaglandin synthetase inhibition.

Pharmacokinetics

Absorption

The mean oral bioavailability of flurbiprofen 100 mg tablets is 96% relative to an oral solution. Flurbiprofen is rapidly and non-stereoselectively absorbed with peak plasma concentrations occurring at about 2 hours (see Table 1). Administration of flurbiprofen with either food or antacids may alter the rate but not the extent of flurbiprofen absorption. Ranitidine has been shown to have no effect on either the rate or extent of flurbiprofen absorption.

Distribution

The apparent volume of distribution (Vz/F) of both R- and S-flurbiprofen is approximately 0.12 L/Kg. Both flurbiprofen enantiomers are more than 99% bound to plasma proteins, primarily albumin. Plasma protein binding is relatively constant for the typical average steady-state concentrations (≤ 10 mcg/mL) achieved with recommended doses. Flurbiprofen is poorly excreted into human milk. The nursing infant dose is predicted to be approximately 0.1 mg/day in the established milk of a woman taking flurbiprofen 200 mg/day (see PRECAUTIONS: Nursing Mothers).

Metabolism

Several flurbiprofen metabolites have been identified in human plasma and urine. These metabolites include 4'-hydroxy-flurbiprofen, 3', 4'-dihydroxy-flurbiprofen, 3'-hydroxy-4'-methoxy-flurbiprofen, their conjugates, and conjugated flurbiprofen. Unlike other arylpropionic acid derivatives (e.g., ibuprofen), metabolism of R-flurbiprofen to S-flurbiprofen is minimal. In vitro studies have demonstrated that cytochrome P450 2C9 plays an important role in the metabolism of flurbiprofen to its major metabolite, 4'-hydroxy-flurbiprofen. The 4'-hydroxy-flurbiprofen metabolite showed little anti-inflammatory activity in animal models of inflammation. Flurbiprofen does not induce enzymes that alter its metabolism.

The total plasma clearance of unbound flurbiprofen is not stereoselective, and clearance of flurbiprofen is independent of dose when used within the therapeutic range.

Excretion

Following dosing with flurbiprofen, less than 3% of flurbiprofen is excreted unchanged in the urine, with about 70% of the dose eliminated in the urine as parent drug and metabolites. Because renal elimination is a significant pathway of elimination of flurbiprofen metabolites, dosing adjustment in patients with moderate or severe renal dysfunction may be necessary to avoid accumulation of flurbiprofen metabolites. The mean terminal disposition half-lives (t1/2) of R- and S-flurbiprofen are similar, about 4.7 and 5.7 hours, respectively. There is little accumulation of flurbiprofen following multiple doses of flurbiprofen.

Table 1. Mean (SD) R, S-Flurbiprofen Pharmacokinetic Parameters Normalized to a 100 mg Dose of Flurbiprofen
Pharmacokinetic; Parameter | Normal Healthy; Adults; (18 to 40 years); N = 15 | Geriatric; Arthritis Patients; (65 to 83 years); N = 13 | End Stage Renal; Disease Patients*; (23 to 42 years); N = 8 | Alcoholic; Cirrhosis Patients; (31 to 61 years); N = 8
Peak; Concentration; (Tg/mL) | 14 (4) | 16 (5) | 9 | 9§
Time of Peak; Concentration; (h) | 1.9 (1.5) | 2.2 (3) | 2.3§ | 1.2§
Urinary Recovery; of Unchanged; Flurbiprofen; (% of Dose) | 2.9 (1.3) | 0.6 (0.6) | 0.02 (0.02) | NA
Area Under the; Curve (AUC); (Tg h/mL) | 83 (20) | 77 (24) | 44§ | 50§
Apparent Volume; of Distribution; (Vz/F, L) | 14 (3) | 12 (5) | 10§ | 14§
Terminal; Disposition; Half-life (t1/2, h) | 7.5 (0.8) | 5.8 (1.9) | 3.3 | 5.4Þ

Special Populations

Pediatric

The pharmacokinetics of flurbiprofen have not been investigated in pediatric patients.

Race

No pharmacokinetic differences due to race have been identified.

Geriatric

Flurbiprofen pharmacokinetics were similar in geriatric arthritis patients, younger arthritis patients, and young healthy volunteers receiving flurbiprofen tablets 100 mg as either single or multiple doses.

Hepatic Insufficiency

Hepatic metabolism may account for > 90% of flurbiprofen elimination, so patients with hepatic disease may require reduced doses of flurbiprofen tablets compared to patients with normal hepatic function. The pharmacokinetics of R- and S-flurbiprofen were similar, however, in alcoholic cirrhosis patients (N = 8) and young healthy volunteers (N = 8) following administration of a single 200 mg dose of flurbiprofen tablets.

Flurbiprofen plasma protein binding may be decreased in patients with liver disease and serum albumin concentrations below 3.1 g/dL (see PRECAUTIONS: General: Hepatic Effects).

Renal Insufficiency

Renal clearance is an important route of elimination for flurbiprofen metabolites, but a minor route of elimination for unchanged flurbiprofen (≤ 3% of total clearance). The unbound clearances of R- and S-flurbiprofen did not differ significantly between normal healthy volunteers (N = 6, 50 mg single dose) and patients with renal impairment (N = 8, inulin clearances ranging from 11 to 43 mL/min, 50 mg multiple doses). Flurbiprofen plasma protein binding may be decreased in patients with renal impairment and serum albumin concentrations below 3.9 g/dL. Elimination of flurbiprofen metabolites may be reduced in patients with renal impairment (see PRECAUTIONS: General: Renal Effects).

Flurbiprofen is not significantly removed from the blood into dialysate in patients undergoing continuous ambulatory peritoneal dialysis.

Drug-Drug Interactions

(see also PRECAUTIONS: Drug Interactions)

Antacids

Administration of flurbiprofen to volunteers under fasting conditions or with antacid suspension yielded similar serum flurbiprofen-time profiles in young adult subjects (n = 12). In geriatric subjects (n = 7), there was a reduction in the rate but not the extent of flurbiprofen absorption.

Aspirin

Concurrent administration of flurbiprofen and aspirin resulted in 50% lower serum flurbiprofen concentrations. This effect of aspirin (which is also seen with other non-steroidal anti-inflammatory drugs) has been demonstrated in patients with rheumatoid arthritis (n = 15) and in healthy volunteers (n = 16) (see PRECAUTIONS: Drug Interactions).

Beta-Adrenergic Blocking Agents

The effect of flurbiprofen on blood pressure response to propranolol and atenolol was evaluated in men with mild uncomplicated hypertension (n = 10). Flurbiprofen pretreatment attenuated the hypotensive effect of a single dose of propranolol but not atenolol. Flurbiprofen did not appear to affect the beta-blocker-mediated reduction in heart rate. Flurbiprofen did not affect the pharmacokinetic profile of either drug (see PRECAUTIONS: Drug Interactions).

Cimetidine, Ranitidine

In normal volunteers (n = 9), pretreatment with cimetidine or ranitidine did not affect flurbiprofen pharmacokinetics, except for a small (13%) but statistically significant increase in the area under the serum concentration curve of flurbiprofen in subjects who received cimetidine.

Digoxin

In studies of healthy males (n = 14), concomitant administration of flurbiprofen and digoxin did not change the steady-state serum levels of either drug.

Diuretics

Studies in healthy volunteers have shown that, like other non-steroidal anti-inflammatory drugs, flurbiprofen can interfere with the effects of furosemide. Although results have varied from study to study, effects have been shown on furosemide-stimulated diuresis, natriuresis, and kaliuresis. Other non-steroidal anti-inflammatory drugs that inhibit prostaglandin synthesis have been shown to interfere with thiazide and potassium-sparing diuretics (see PRECAUTIONS: Drug Interactions).

Lithium

In a study of 11 women with bipolar disorder receiving lithium carbonate at a dosage of 600 mg to 1200 mg/day, administration of 100 mg flurbiprofen every 12 hours increased plasma lithium concentrations by 19%. Four of 11 patients experienced a clinically important increase (> 25% or > 0.2 mmol/L). Non-steroidal anti-inflammatory drugs have also been reported to decrease the renal clearance of lithium by about 20% (see PRECAUTIONS: Drug Interactions).

Methotrexate

In a study of six adult arthritis patients, coadministration of methotrexate (10 to 25 mg/dose) and flurbiprofen (300 mg/day) resulted in no observable interaction between these two drugs.

Oral Hypoglycemic Agents

In a clinical study, flurbiprofen was administered to adult diabetics who were already receiving glyburide (n = 4), metformin (n = 2), chlorpropamide with phenformin (n = 3), or glyburide with phenformin (n = 6). Although there was a slight reduction in blood sugar concentrations during concomitant administration of flurbiprofen and hypoglycemic agents, there were no signs or symptoms of hypoglycemia.

INDICATIONS AND USAGE

Carefully consider the potential benefits and risks of flurbiprofen tablets and other treatment options before deciding to use flurbiprofen tablets. Use the lowest effective dose for the shortest duration consistent with individual patient treatment goals (see WARNINGS).

Flurbiprofen tablets are indicated:

- For relief of the signs and symptoms of rheumatoid arthritis.
- For relief of the signs and symptoms of osteoarthritis.

CONTRAINDICATIONS

Flurbiprofen tablets are contraindicated in patients with known hypersensitivity to flurbiprofen tablets or the excipients (see DESCRIPTION).

Flurbiprofen should not be given to patients who have experienced asthma, urticaria, or allergic-type reactions after taking aspirin or other non-steroidal anti-inflammatory drugs. Severe, rarely fatal, anaphylactic-like reactions to non-steroidal anti-inflammatory drugs have been reported in such patients (see WARNINGS: Anaphylactoid Reactions and PRECAUTIONS: General: Preexisting Asthma).

Flurbiprofen is contraindicated for the treatment of perioperative pain in the setting of coronary artery bypass graft (CABG) surgery (see WARNINGS).

WARNINGS

Cardiovascular Effects

Cardiovascular Thrombotic Events

Clinical trials of several COX-2 selective and nonselective NSAIDs of up to three years duration have shown an increased risk of serious cardiovascular (CV) thrombotic events, myocardial infarction, and stroke, which can be fatal. All NSAIDs, both COX-2 selective and nonselective, may have a similar risk. Patients with known CV disease or risk factors for CV disease may be at greater risk. To minimize the potential risk for an adverse CV event in patients treated with an NSAID, the lowest effective dose should be used for the shortest duration possible. Physicians and patients should remain alert for the development of such events, even in the absence of previous CV symptoms. Patients should be informed about the signs and/or symptoms of serious CV events and the steps to take if they occur.

There is no consistent evidence that concurrent use of aspirin mitigates the increased risk of serious CV thrombotic events associated with NSAID use. The concurrent use of aspirin and an NSAID does increase the risk of serious GI events (see WARNINGS: Gastrointestinal Effects).

Two large, controlled, clinical trials of a COX-2 selective NSAID for the treatment of pain in the first 10 to 14 days following CABG surgery found an increased incidence of myocardial infarction and stroke (see CONTRAINDICATIONS).

Hypertension

NSAIDs, including flurbiprofen, can lead to onset of new hypertension or worsening of preexisting hypertension, either of which may contribute to the increased incidence of CV events. Patients taking thiazides or loop diuretics may have impaired response to these therapies when taking NSAIDs. NSAIDs, including flurbiprofen, should be used with caution in patients with hypertension. Blood pressure (BP) should be monitored closely during the initiation of NSAID treatment and throughout the course of therapy.

Congestive Heart Failure and Edema

Fluid retention and edema have been observed in some patients taking NSAIDs. Flurbiprofen should be used with caution in patients with fluid retention or heart failure.

Gastrointestinal Effects

Risk of Ulceration, Bleeding, and Perforation

NSAIDs, including flurbiprofen, can cause serious gastrointestinal (GI) adverse events including inflammation, bleeding, ulceration, and perforation of the stomach, small intestine, or large intestine, which can be fatal. These serious adverse events can occur at any time, with or without warning symptoms, in patients treated with NSAIDs. Only one in five patients, who develop a serious upper GI adverse event on NSAID therapy is symptomatic. Upper GI ulcers, gross bleeding, or perforation caused by NSAIDs occur in approximately 1% of patients treated for 3 to 6 months, and in about 2% to 4% of patients treated for one year. These trends continue with longer duration of use, increasing the likelihood of developing a serious GI event at some time during the course of therapy. However, even short-term therapy is not without risk.

NSAIDs should be prescribed with extreme caution in those with a prior history of ulcer disease or gastrointestinal bleeding. Patients with a prior history of peptic ulcer disease and/or gastrointestinal bleeding who use NSAIDs have a greater than 10-fold increased risk for developing a GI bleed compared to patients treated with neither of these risk factors. Other factors that increase the risk of GI bleeding in patients treated with NSAIDs include concomitant use of oral corticosteroids or anticoagulants, longer duration of NSAID therapy, smoking, use of alcohol, older age, and poor general health status. Most spontaneous reports of fatal GI events are in elderly or debilitated patients and therefore, special care should be taken in treating this population.

To minimize the potential risk for an adverse GI event in patients treated with an NSAID, the lowest effective dose should be used for the shortest possible duration. Patients and physicians should remain alert for signs and symptoms of GI ulcerations and bleeding during NSAID therapy and promptly initiate additional evaluation and treatment if a serious GI event is suspected. This should include discontinuation of the NSAID until a serious GI adverse event is ruled out. For high risk patients, alternate therapies that do not involve NSAIDs should be considered.

Renal Effects

Long-term administration of NSAIDs has resulted in renal papillary necrosis and other renal injury. Renal toxicity has also been seen in patients in whom renal prostaglandins have a compensatory role in the maintenance of renal perfusion. In these patients, administration of a non-steroidal anti-inflammatory drug may cause a dose dependent reduction in prostaglandin formation and, secondarily, in renal blood flow, which may precipitate overt renal decompensation. Patients at greatest risk of this reaction are those with impaired renal function, heart failure, liver dysfunction, those taking diuretics and ACE inhibitors, and the elderly. Discontinuation of NSAID therapy is usually followed by recovery to the pretreatment state.

Advanced Renal Disease

In clinical studies, the elimination half-life of flurbiprofen was unchanged in patients with renal impairment. Flurbiprofen metabolites are eliminated primarily by the kidneys. Elimination of 4'-hydroxy-flurbiprofen was reduced in patients with moderate to severe renal impairment. Therefore, treatment with flurbiprofen is not recommended in these patients with advanced renal disease. If flurbiprofen therapy must be initiated, close monitoring of the patients renal function is advisable (see CLINICAL PHARMACOLOGY).

Anaphylactoid Reactions

As with other NSAIDs, anaphylactoid reactions may occur in patients without known prior exposure to flurbiprofen. Flurbiprofen should not be given to patients with the aspirin triad. This symptom complex typically occurs in asthmatic patients who experience rhinitis with or without nasal polyps, or who exhibit severe, potentially fatal bronchospasm after taking aspirin or other NSAIDs (see CONTRAINDICATIONS and PRECAUTIONS: General: Preexisting Asthma). Emergency help should be sought in cases where an anaphylactoid reaction occurs.

Pregnancy

In late pregnancy, as with other NSAIDs, flurbiprofen should be avoided because it may cause premature closure of the ductus arteriosus.

PRECAUTIONS

General

Flurbiprofen cannot be expected to substitute for corticosteroids or to treat corticosteroid insufficiency. Abrupt discontinuation of corticosteroids may lead to disease exacerbation. Patients on prolonged corticosteroid therapy should have their therapy tapered slowly if a decision is made to discontinue corticosteroids.

The pharmacological activity of flurbiprofen in reducing fever and inflammation may diminish the utility of these diagnostic signs in detecting complications of presumed noninfectious, painful conditions.

Hepatic Effects

Borderline elevations of one or more liver tests may occur in up to 15% of patients taking non-steroidal anti-inflammatory drugs, including flurbiprofen. These laboratory abnormalities may progress, may remain unchanged, or may be transient with continuing therapy. Notable elevations of ALT or AST (approximately three or more times the upper limit of normal) have been reported in approximately 1% of patients in clinical trials with non-steroidal anti-inflammatory drugs. In addition, rare cases of severe hepatic reactions, including jaundice, fulminant hepatitis, liver necrosis, and hepatic failure, some of them with fatal outcomes have been reported.

A patient with symptoms and/or signs suggesting liver dysfunction, or with abnormal liver test values, should be evaluated for evidence of the development of a more severe hepatic reaction while on therapy with flurbiprofen. If clinical signs and symptoms consistent with liver disease develop, or if systemic manifestations occur (e.g., eosinophilia, rash, etc.), flurbiprofen should be discontinued.

Hematological Effects

Anemia is sometimes seen in patients receiving non-steroidal anti-inflammatory drugs, including flurbiprofen. This may be due to fluid retention, GI blood loss, or an incompletely described effect upon erythropoiesis. Patients on long-term treatment with non-steroidal anti-inflammatory drugs, including flurbiprofen, should have their hemoglobin or hematocrit checked periodically even if they do not exhibit any signs or symptoms of anemia.

Non-steroidal anti-inflammatory drugs inhibit platelet aggregation and have been shown to prolong bleeding time in some patients. Unlike aspirin, their effect on platelet function is quantitatively less, of shorter duration, and reversible. Flurbiprofen does not generally affect platelet counts, prothrombin time (PT), or partial thromboplastin time (PTT). Patients receiving flurbiprofen who may be adversely affected by alterations in platelet function, such as those with coagulation disorders or patients receiving anticoagulants, should be carefully monitored.

Preexisting Asthma

Patients with asthma may have aspirin-sensitive asthma. The use of aspirin in patients with aspirin-sensitive asthma has been associated with severe bronchospasm which can be fatal. Since cross-reactivity, including bronchospasm, between aspirin and other non-steroidal anti-inflammatory drugs has been reported in such aspirin-sensitive patients, flurbiprofen should not be administered to patients with this form of aspirin sensitivity and should be used with caution in patients with preexisting asthma.

Vision Changes

Blurred and/or diminished vision has been reported with the use of flurbiprofen and other non-steroidal anti-inflammatory drugs. Patients experiencing eye complaints should have ophthalmologic examinations.

Information for Patients

Patients should be informed of the following information before initiating therapy with an NSAID and periodically during the course of ongoing therapy. Patients should also be encouraged to read the NSAID Medication Guide that accompanies each prescription dispensed.

- Flurbiprofen, like other NSAIDs, may cause CV side effects, such as MI or stroke, which may result in hospitalization and even death. Although serious CV events can occur without warning symptoms, patients should be alert for the signs and symptoms of chest pain, shortness of breath, weakness, slurring of speech, and should ask for medical advice when observing any indicative sign or symptoms. Patients should be apprised of the importance of this follow-up (see WARNINGS: Cardiovascular Effects).
- Flurbiprofen, like other NSAIDs, can cause GI discomfort and, rarely, serious GI side effects, such as ulcers and bleeding, which may result in hospitalization and even death. Although serious GI tract ulcerations and bleeding can occur without warning symptoms, patients should be alert for the signs and symptoms of ulcerations and bleeding, and should ask for medical advice when observing any indicative sign or symptoms including epigastric pain, dyspepsia, melena, and hematemesis. Patients should be apprised of the importance of this follow-up (see WARNINGS: Gastrointestinal Effects: Risk of Ulceration, Bleeding, and Perforation).
- Flurbiprofen, like other NSAIDs, can cause serious skin side effects such as exfoliative dermatitis, SJS, and TEN, which may result in hospitalizations and even death. Although serious skin reactions may occur without warning, patients should be alert for the signs and symptoms of skin rash and blisters, fever, or other signs of hypersensitivity such as itching, and should ask for medical advice when observing any indicative signs or symptoms. Patients should be advised to stop the drug immediately if they develop any type of rash and contact their physicians as soon as possible.
- Patients should promptly report signs or symptoms of unexplained weight gain or edema to their physicians.
- Patients should be informed of the warning signs and symptoms of hepatotoxicity (e.g., nausea, fatigue, lethargy, pruritus, jaundice, right upper quadrant tenderness and “flu-like” symptoms). If these occur, patients should be instructed to stop therapy and seek immediate medical therapy.
- Patients should be informed of the signs of an anaphylactoid reaction (e.g. difficulty breathing, swelling of the face or throat). If these occur, patients should be instructed to seek immediate emergency help (see WARNINGS).
- In late pregnancy, as with other NSAIDs, flurbiprofen should be avoided because it may cause premature closure of the ductus arteriosus.

Laboratory Tests

Because serious GI tract ulcerations and bleeding can occur without warning symptoms, physicians should monitor for signs or symptoms of GI bleeding. Patients on long-term treatment with non-steroidal anti-inflammatory drugs should have their CBC and chemistry profile checked periodically. If clinical signs and symptoms consistent with liver or renal disease develop, systemic manifestations occur (e.g., eosinophilia, rash, etc.) or abnormal liver tests persist or worsen, flurbiprofen should be discontinued.

Drug Interactions

ACE Inhibitors

Reports suggest that non-steroidal anti-inflammatory drugs may diminish the antihypertensive effect of ACE inhibitors. These interactions should be given consideration in patients taking non-steroidal anti-inflammatory drugs concomitantly with ACE inhibitors.

Anticoagulants

The effects of warfarin and NSAIDs on GI bleeding are synergistic, such that users of both drugs together have a risk of serious GI bleeding higher than users of either drug alone. The physician should be cautious when administering flurbiprofen to patients taking warfarin or other anticoagulants.

Aspirin

Concurrent administration of aspirin lowers serum flurbiprofen concentrations (see CLINICAL PHARMACOLOGY: Drug-Drug Interactions). The clinical significance of this interaction is not known; however, as with other NSAIDs, concomitant administration of flurbiprofen and aspirin is not generally recommended because of the potential for increased adverse effects.

Beta-Adrenergic Blocking Agents

Flurbiprofen attenuated the hypotensive effect of propranolol but not atenolol (see CLINICAL PHARMACOLOGY: Drug-Drug Interactions). The mechanism underlying this interference is unknown. Patients taking both flurbiprofen and a beta-blocker should be monitored to ensure that a satisfactory hypotensive effect is achieved.

Diuretics

Clinical studies, as well as post-marketing observations, have shown that flurbiprofen can reduce the natriuretic effect of furosemide and thiazides in some patients. This response has been attributed to inhibition of renal prostaglandin synthesis. During concomitant therapy with NSAIDs, the patient should be observed closely for signs of renal failure (see WARNINGS: Renal Effects), as well as diuretic efficacy.

Lithium

NSAIDs have produced an elevation of plasma lithium levels and a reduction in renal lithium clearance. The mean minimum lithium concentration increased 15% and the renal clearance was decreased by approximately 20%.

These effects have been attributed to inhibition of renal prostaglandin synthesis by the non-steroidal anti-inflammatory drugs. Thus, when non-steroidal anti-inflammatory drugs and lithium are administered concurrently, subjects should be observed carefully for signs of lithium toxicity.

Methotrexate

Non-steroidal anti-inflammatory drugs have been reported to competitively inhibit methotrexate accumulation in rabbit kidney slices. This may indicate that they could enhance the toxicity of methotrexate. Caution should be used when non-steroidal anti-inflammatory drugs are administered concomitantly with methotrexate.

Pregnancy

Teratogenic Effects. Pregnancy Category C

Reproductive studies conducted in rats and rabbits have not demonstrated evidence of developmental abnormalities. However, animal reproduction studies are not always predictive of human response. There are no adequate and well controlled studies in pregnant women. Flurbiprofen should be used in pregnancy only if the potential benefit justifies the potential risk to the fetus.

Nonteratogenic Effects

Because of the known effects of non-steroidal anti-inflammatory drugs on the fetal cardiovascular system (closure of ductus arteriosus), use during late pregnancy should be avoided.

Labor and Delivery

In rat studies with non-steroidal anti-inflammatory drugs, as with other drugs known to inhibit prostaglandin synthesis, an increased incidence of dystocia, delayed parturition, and decreased pup survival occurred. The effects of flurbiprofen on labor and delivery in pregnant women are unknown.

Nursing Mothers

Concentrations of flurbiprofen in breast milk and plasma of nursing mothers suggest that a nursing infant could receive approximately 0.10 mg flurbiprofen per day in the established milk of a woman taking flurbiprofen 200 mg/day. Because of possible adverse effects of prostaglandin-inhibiting drugs on neonates, a decision should be made whether to discontinue nursing or to discontinue the drug, taking into account the importance of the drug to the mother.

Pediatric Use

Safety and effectiveness in pediatric patients have not been established.

Geriatric Use

As with any NSAID, caution should be exercised in treating the elderly (65 years and older). Clinical experience with flurbiprofen suggests that elderly patients may have a higher incidence of gastrointestinal complaints than younger patients, including ulceration, bleeding, flatulence, bloating, and abdominal pain. To minimize the potential risk for gastrointestinal events, the lowest effective dose should be used for the shortest possible duration (see WARNINGS: Gastrointestinal Effects). Likewise, elderly patients are at greater risk of developing renal decompensation (see WARNINGS: Renal Effects).

The pharmacokinetics of flurbiprofen do not seem to differ in elderly patients from those in younger individuals (see CLINICAL PHARMACOLOGY: Special Populations). The rate of absorption of flurbiprofen was reduced in elderly patients who also received antacids, although the extent of absorption was not affected (see CLINICAL PHARMACOLOGY: Drug-Drug Interactions).

ADVERSE REACTIONS

TABLE 2. Reported adverse events in patients receiving flurbiprofen or other non-steroidal anti-inflammatory drugs
Reported in patients treated with flurbiprofen |  |  | Reported in patients; treated with other; products but not; flurbiprofen
Incidence of 1%; or greater | Incidence < 1% -; Causal Relationship; Probable | Incidence < 1% -; Causal Relationship; Unknown † | Reported in patients; treated with other; products but not; flurbiprofen
BODY AS A WHOLE; edema | anaphylactic; reaction; chills; fever |  | < 1%:; death; infection; sepsis
CARDIOVASCULAR; SYSTEM | congestive heart; failure; hypertension; vascular diseases; vasodilation | angina pectoris; arrhythmias; myocardial infarction | < 1%:; hypotension; palpitations; syncope; tachycardia; vasculitis
DIGESTIVE SYSTEM; abdominal pain; constipation; diarrhea; dyspepsia/heartburn; elevated liver enzymes; flatulence; GI bleeding; nausea; vomiting | bloody diarrhea; esophageal disease; gastric/peptic ulcer; disease; gastritis; jaundice; (cholestatic and; noncholestatic); hematemesis; hepatitis; stomatitis/glossitis | appetite changes; cholecystitis; colitis; dry mouth; exacerbation of; inflammatory; bowel disease; periodontal abscess; small intestine; inflammation with; loss of blood and; protein | > 1%:; GI perforation; GI ulcers; (gastric/duodenal); < 1%:; eructation; liver failure; pancreatitis
HEMIC AND LYMPHATIC; SYSTEM | aplastic anemia; (including; agranulocytosis; or pancytopenia); decrease in; hemoglobin and; hematocrit; ecchymosis/purpura; eosinophilia; hemolytic anemia; iron deficiency; anemia; leucopenia; thrombocytopenia | lymphadenopathy | > 1%:; anemia; increased bleeding; time; < 1%:; melena; rectal bleeding
METABOLIC AND; NUTRITIONAL SYSTEM; body weight changes | hyperuricemia | hyperkalemia | < 1%:; hyperglycemia
NERVOUS SYSTEM; headache; nervousness and other; manifestations of; central nervous; system (CNS); stimulation (e.g.,; anxiety, insomnia,; increased reflexes,; tremor); symptoms associated; with CNS inhibition; (e.g., amnesia, asthenia,; depression, malaise,; somnolence) | ataxia; cerebrovascular; ischemia; confusion; paresthesia; twitching | convulsion; cerebrovascular; accident; emotional lability; hypertonia; meningitis; myasthenia; subarachnoid; hemorrhage | < 1%:; coma; dream abnormalities; drowsiness; hallucinations
RESPIRATORY SYSTEM; rhinitis | asthma; epistaxis | bronchitis; dyspnea; hyperventilation; laryngitis; pulmonary embolism; pulmonary infarct | < 1%:; pneumonia; respiratory; depression
SKIN AND APPENDAGES; Rash | angioedema; eczema; exfoliative; dermatitis; photosensitivity; pruritus; toxic epidermal; necrolysis; urticaria | alopecia; dry skin; herpes simplex/zoster; nail disorder; sweating | < 1%:; erythema; multiforme; Stevens Johnson; Syndrome
SPECIAL SENSES; changes in vision; dizziness/vertigo; tinnitus | conjunctivitis; parosmia | changes in taste; corneal opacity; ear disease; glaucoma; retinal hemorrhage; retrobulbar neuritis; transient hearing loss | > 1%:; pruritus; < 1%:; hearing impairment
UROGENITAL SYSTEM; signs and symptoms; suggesting urinary; tract infection | hematuria; interstitial nephritis; renal failure | menstrual; disturbances; prostate disease; vaginal and uterine; hemorrhage; vulvovaginitis | > 1%:; abnormal renal; function; < 1%:; dysuria; oliguria; polyuria; proteinuria

OVERDOSAGE

Symptoms following acute overdoses with non-steroidal anti-inflammatory drugs are usually limited to lethargy, drowsiness, nausea, vomiting, and epigastric pain, which are generally reversible with supportive care. Gastrointestinal bleeding can occur. Hypertension, acute renal failure, respiratory depression and coma may occur, but are rare. Anaphylactoid reactions have been reported with therapeutic ingestion of non-steroidal anti-inflammatory drugs, and may occur following an overdose.

Patients should be managed by symptomatic and supportive care following overdose with a non-steroidal anti-inflammatory drug. There are no specific antidotes. Emesis and/or activated charcoal (60 g to 100 g in adults, 1 to 2 g/kg in children) and/or osmotic cathartic may be indicated in patients seen within 4 hours of ingestion with symptoms, or following a large overdose (5 to 10 times the usual dose). Forced diuresis, alkalization of urine, hemodialysis, or hemoperfusion may not be useful due to high protein binding.

DOSAGE AND ADMINISTRATION

Carefully consider the potential benefits and risks of flurbiprofen and other treatment options before deciding to use flurbiprofen. Use the lowest effective dose for the shortest duration consistent with individual patient treatment goals (see WARNINGS).

After observing the response to initial therapy with flurbiprofen, the dose and frequency should be adjusted to suit an individual patient’s needs.

For relief of the signs and symptoms of rheumatoid arthritis or osteoarthritis, the recommended starting dose of flurbiprofen is 200 mg to 300 mg per day, divided for administration two, three, or four times a day. The largest recommended single dose in a multiple-dose daily regimen is 100 mg.

HOW SUPPLIED

Flurbiprofen tablets, USP are available containing 100 mg of flurbiprofen, USP.

The 100 mg tablets are film-coated beige, round, unscored, tablets debossed with M over 93 on one side of the tablet and blank on the other side. They are available as follows:

Bottles of 20 | NDC 54868-3362-0
Bottles of 60 | NDC 54868-3362-1
Bottles of 100 | NDC 54868-3362-2

Store at 20° to 25°C (68° to 77°F). [See USP Controlled Room Temperature.]

Protect from light.

Dispense in a tight, light-resistant container as defined in the USP using a child-resistant closure.

PHARMACIST: Dispense a Medication Guide with each prescription.

Mylan Pharmaceuticals Inc.
Morgantown, WV 26505

REVISED JUNE 2009
FRB:R9mc

Relabeling and Repackaging by:
Physicians Total Care, Inc.
Tulsa, Oklahoma 74146

Medication Guide for Non-Steroidal Anti-Inflammatory Drugs (NSAIDs)

(See the end of this Medication Guide for a list of prescription NSAID medicines.)

What is the most important information I should know about medicines called Non-Steroidal Anti-Inflammatory Drugs (NSAIDs)?

NSAID medicines may increase the chance of a heart attack or stroke that can lead to death. This chance increases:

- with longer use of NSAID medicines
- in people who have heart disease

NSAID medicines should never be used right before or after a heart surgery called a “coronary artery bypass graft (CABG).”

NSAID medicines can cause ulcers and bleeding in the stomach and intestines at any time during treatment. Ulcers and bleeding:

- can happen without warning symptoms
- may cause death
  The chance of a person getting an ulcer or bleeding increases with:
    - taking medicines called “corticosteroids” and “anticoagulants”
    - longer use
    - smoking
    - drinking alcohol
    - older age
    - having poor health

NSAID medicines should only be used:

- exactly as prescribed
- at the lowest dose possible for your treatment
- for the shortest time needed

What are Non-Steroidal Anti-Inflammatory Drugs (NSAIDs)?

NSAID medicines are used to treat pain and redness, swelling, and heat (inflammation) from medical conditions such as:

- different types of arthritis
- menstrual cramps and other types of short-term pain

Who should not take a Non-Steroidal Anti-Inflammatory Drug (NSAID)?

Do not take an NSAID medicine:

- if you had an asthma attack, hives, or other allergic reaction with aspirin or any other NSAID medicine
- for pain right before or after heart bypass surgery

Tell your healthcare provider:

- about all of your medical conditions.
- about all of the medicines you take. NSAIDs and some other medicines can interact with each other and cause serious side effects. Keep a list of your medicines to show to your healthcare provider and pharmacist.
- if you are pregnant. NSAID medicines should not be used by pregnant women late in their pregnancy.
- if you are breastfeeding. Talk to your doctor.

What are the possible side effects of Non-Steroidal Anti-Inflammatory Drugs (NSAIDs)?

Serious side effects include:

- heart attack
- stroke
- high blood pressure
- heart failure from body swelling (fluid retention)
- kidney problems including kidney failure
- bleeding and ulcers in the stomach and intestine
- low red blood cells (anemia)
- life-threatening skin reactions
- life-threatening allergic reactions
- liver problems including liver failure
- asthma attacks in people who have asthma

Other side effects include:

- stomach pain
- constipation
- diarrhea
- gas
- heart burn
- nausea
- vomiting
- dizziness

Get emergency help right away if you have any of the following symptoms:

- shortness of breath or trouble breathing
- chest pain
- weakness in one part or side of your body
- slurred speech
- swelling of the face or throat

Stop your NSAID medicine and call your healthcare provider right away if you have any of the following symptoms:

- nausea
- more tired or weaker than usual
- itching
- your skin or eyes look yellow
- stomach pain
- flu-like symptoms
- vomit blood
- there is blood in your bowel movement or it is black and sticky like tar
- unusual weight gain
- skin rash or blisters with fever
- swelling of the arms and legs, hands and feet

These are not all the side effects with NSAID medicines. Talk to your healthcare provider or pharmacist for more information about NSAID medicines.

Call your doctor for medical advice about side effects. You may report side effects to FDA at 1-800-FDA-1088.

Other information about Non-Steroidal Anti-Inflammatory Drugs (NSAIDs)

- Aspirin is an NSAID medicine but it does not increase the chance of a heart attack. Aspirin can cause bleeding in the brain, stomach, and intestines. Aspirin can also cause ulcers in the stomach and intestines.
- Some of these NSAID medicines are sold in lower doses without a prescription (over-the-counter). Talk to your healthcare provider before using over-the-counter NSAIDs for more than 10 days.

NSAID medicines that need a prescription
Generic Name | Tradename
Celecoxib | Celebrex
Diclofenac | Cataflam, Voltaren, Arthrotec (combined with misoprostol)
Diflunisal | Dolobid
Etodolac | Lodine, Lodine XL
Fenoprofen | Nalfon, Nalfon 200
Flurbiprofen | Ansaid
Ibuprofen | Motrin, Tab-Profen, Vicoprofen (combined with hydrocodone), Combunox (combined with oxycodone)
Indomethacin | Indocin, Indocin SR, Indo-Lemmon, Indomethagan
Ketoprofen | Oruvail
Ketorolac | Toradol
Mefenamic Acid | Ponstel
Meloxicam | Mobic
Nabumetone | Relafen
Naproxen | Naprosyn, Anaprox, Anaprox DS, EC-Naproxyn, Naprelan, Naprapac (copackaged with lansoprazole)
Oxaprozin | Daypro
Piroxicam | Feldene
Sulindac | Clinoril
Tolmetin | Tolectin, Tolectin DS, Tolectin 600

This Medication Guide has been approved by the U.S. Food and Drug Administration.

Revised 06/2009

PACKAGE LABEL

PRINCIPAL DISPLAY PANEL - 100 mg

ATTENTION:
Dispense with
Medication Guide

FLURBIPROFEN
TABLETS, USP
100 mg

(Rx only)

Each tablet contains:
Flurbiprofen, USP . . . . 100 mg

Dispense in a tight, light-resistant
container as defined in the USP
using a child-resistant closure.

Keep container tightly closed.

Keep this and all medication
out of the reach of children.

Store at 20° to 25°C (68° to 77°F).
[See USP for Controlled Room
Temperature.]

Protect from light.

Usual Dosage: See accompanying
prescribing information.